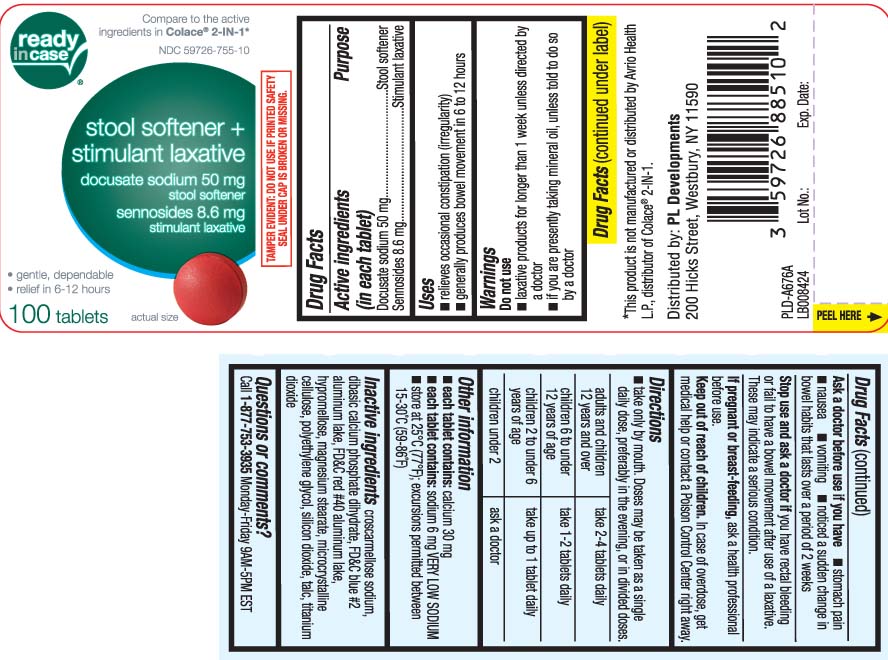 DRUG LABEL: Stool Softener Laxative
NDC: 59726-755 | Form: TABLET
Manufacturer: P & L Development, LLC
Category: otc | Type: HUMAN OTC DRUG LABEL
Date: 20260126

ACTIVE INGREDIENTS: DOCUSATE SODIUM 50 mg/1 1; SENNOSIDES 8.6 mg/1 1
INACTIVE INGREDIENTS: CROSCARMELLOSE SODIUM; DIBASIC CALCIUM PHOSPHATE DIHYDRATE; FD&C RED NO. 40; HYPROMELLOSES; MAGNESIUM STEARATE; CELLULOSE, MICROCRYSTALLINE; POLYETHYLENE GLYCOL, UNSPECIFIED; SILICON DIOXIDE; TALC; TITANIUM DIOXIDE; ALUMINUM OXIDE; FD&C BLUE NO. 2

Drug Facts

Active ingredients (in each tablet)

Docusate sodium 50 mg

Sennosides 8.6 mg

Purpose

Stool softener

Stimulant laxative

Uses

- relieves occasional constipation (irregularity)
- generally produces bowel movement in 6 to12 hours

Warnings

Do not use

- laxative products for longer than 1 week unless told to do so by a doctor
- if you are presently taking mineral oil, unless told to do so by a doctor

Ask a doctor before use if you have

- stomach pain
- nausea
- vomiting
- noticed a sudden change in bowel habits that lasts over a period of 2 weeks

Stop use and ask a doctor if

you have rectal bleeding or fail to have a bowel movement after use of a laxative.

These could be signs of a serious condition.

If pregnant or breast-feeding,

ask a health professional before use.

Keep out of reach of children.

In case of overdose, get medical help or contact a Poison Control Center right away.

Directions

- Take only by mouth. Doses may be taken as a single daily dose, preferably in the evening, or in divided doses.

adults and children 12 years and older | take 2-4 tablets daily
children 6 to under 12 years of age | take 1-2 tablets daily
children 2 to under 6 years of age | take up to 1 tablet daily
children under 2 | ask a doctor

Other information

- each tablet contains: calcium 30 mg
- each tablet contains: sodium 6 mg VERY LOW SODIUM
- store at 25ºC (77ºF); excursions permitted between 15-30ºC (59-86ºF)

Inactive ingredients

croscarmellose sodium, dibasic calcium phosphate dihydrate, FD&C blue #2 aluminum lake, FD&C red #40 aluminum lake, hypromellose, magnesium stearate, microcrystalline cellulose, polyethylene glycol, silcon dioxide, talc, titanium dioxide

Questions or comments?

Call 1-877-753-3935 Monday-Friday 9AM-5PM EST

Principal Display Panel

Compare to the active ingredients in Colace® 2-IN-1*

Stool Softener + Stimulant Laxative

docusate sodium 50 mg

stool softener

sennosides 8.6 mg

stimulant laxative

- gentle, dependable
- relief in 6 to 12 hours

tablets

*This product is not manufactured of distributed by Avrio Health L.P., distributor of Colace® 2-IN1

TAMPER EVIDENT: DO NOT USE IF PRINTED SAFETY SEAL UNDER CAP IS BROKEN OR MISSING

Distributed by: PL Developments

200 Hicks Street, Westbury, NY 11590

Product Label

READYinCASE Stool Softener Laxative